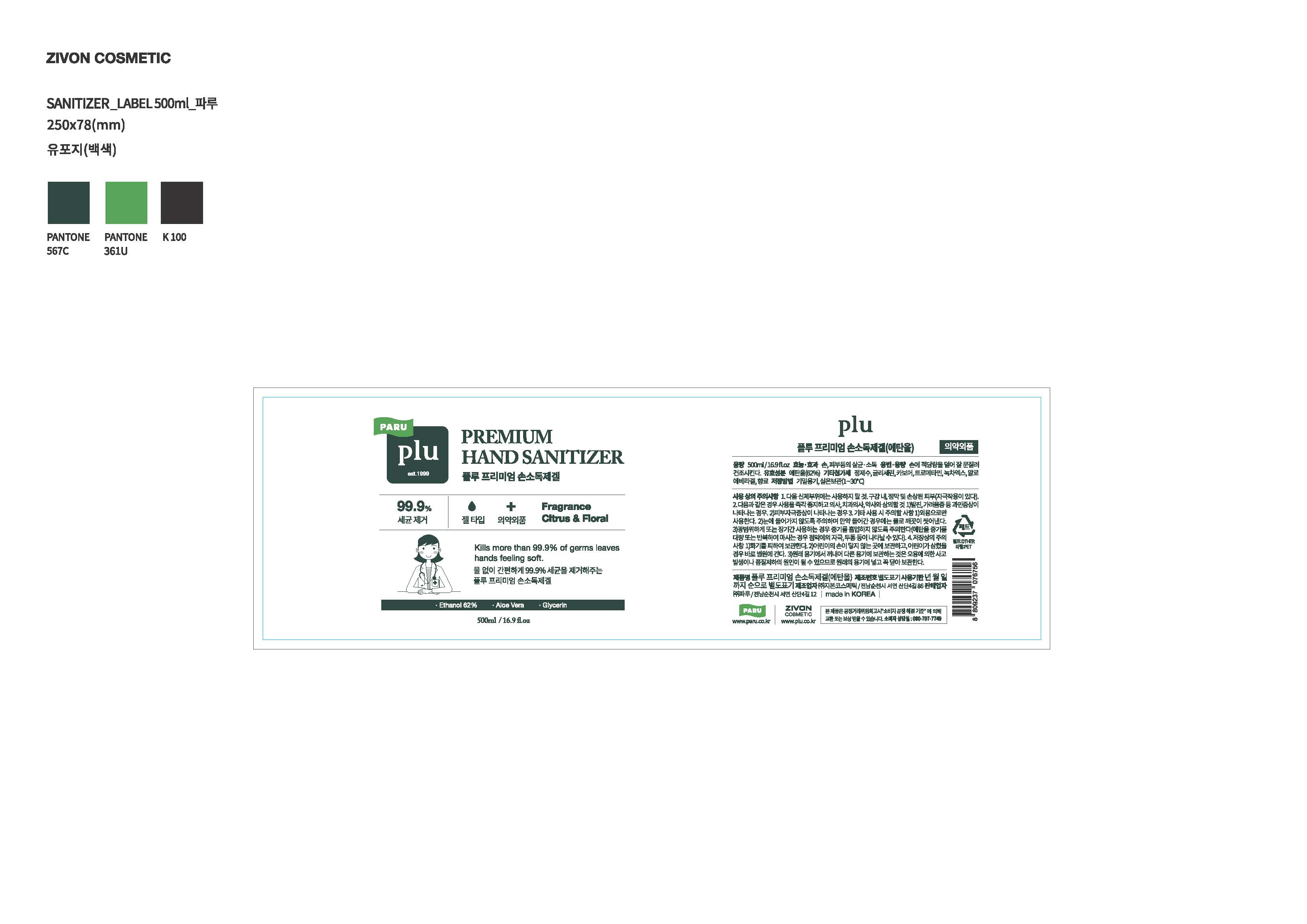 DRUG LABEL: Plu Premium Hand Sanitizer
NDC: 71503-114 | Form: GEL
Manufacturer: Zivon Cosmetic Co., Ltd.
Category: otc | Type: HUMAN OTC DRUG LABEL
Date: 20200507

ACTIVE INGREDIENTS: ALCOHOL 310 mL/500 mL
INACTIVE INGREDIENTS: ALOE; WATER; GLYCERIN

Drug Facts

ACTIVE INGREDIENT

Alcohol 62%

INACTIVE INGREDIENT

Glycerin, Carboner, Tromethamine, Aloe Barbadensis Leaf Extract, Camellia Sinensis Leaf Extract, Fragrance, Water

PURPOSE

Antiseptic

KEEP OUT OF REACH OF THE CHILDREN

INDICATIONS AND USAGE

For the external use only

WARNINGS

For external use only.

Flammable, keep away from fire or flame.

When using this product keep out of eyes. If contact with eyes occurs, rinse promptly and thoroughly with water.

Stop use and ask a doctor if significant irritation or sensitization develops.

Keep out of reach of children. If swallowed, get medical help or contact a Poison Control Center right away.

DOSAGE AND ADMINISTRATION

Apply to clean, dry hands.

Apply sufficient amount to thoroughly wet all surfaces of hands and fingers.

Rub onto hands until dry.

Supervise children in the use of this product.